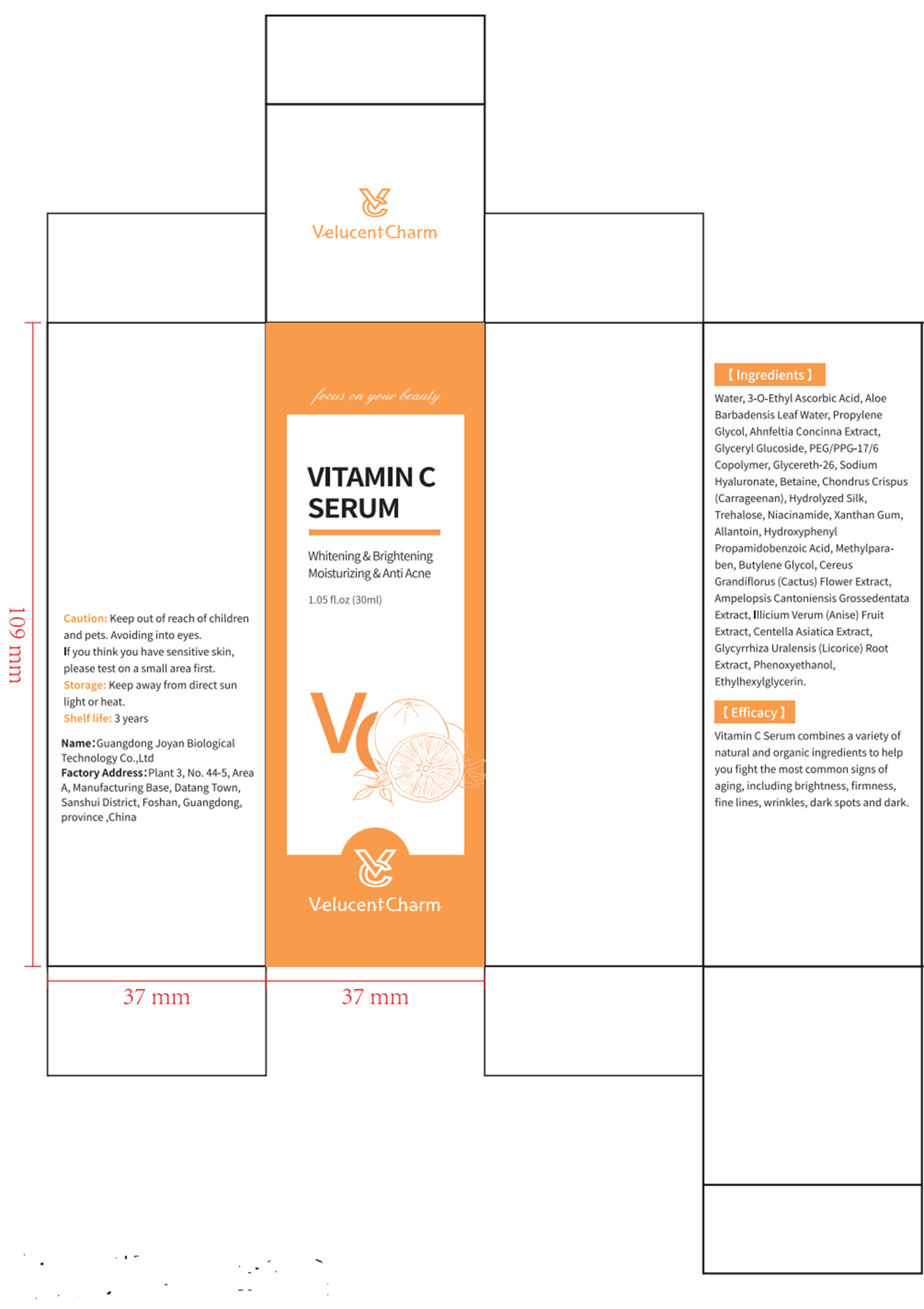 DRUG LABEL: Vitamin C Serum
NDC: 84716-123 | Form: SOLUTION, CONCENTRATE
Manufacturer: Shenzhen Boyang E-commerce Co.
Category: otc | Type: HUMAN OTC DRUG LABEL
Date: 20240925

ACTIVE INGREDIENTS: 3-O-ETHYL ASCORBIC ACID 1.4925 g/30 g; GLYCERIN 0.072 g/30 g; GLYCERYL GLUCOSIDE 0.072 g/30 g
INACTIVE INGREDIENTS: WATER 27.435705 g/30 g

ACTIVE INGREDIENTS

ALOE BARBADENSIS LEAF WATER 0.5%
PROPYLENE GLYCOL 0.41%
AHNFELTIOPSIS CONCINNA EXTRACT 0.316%
GLYCERYL GLUCOSIDE 0.24%
GLYCERIN 0.24%

3-o-ETHYL ASCORBIC ACID 4.975%

PURPOSE

Vitamin C Serum combines a variety of natural and organic ingredients to help you fight the most common signs of aging,including brightness, firmness,fine lines, wrinkles, dark spots and dark.

Uses

Apply one drop on clean skin before your moisturizer and smooth in gently all over face.

Warnings

Keep out of reach of children and pets.

Avoiding into eyes.

If you think you have sensitive skin,please test on a small area first.

Stop use and ask a doctor if

lt is recommended to have a skin test (inside the wrist orbehind the ear) before use.If you feel uncomfortable,please stop using it.

Do not use

on damaged or broken skin

Keep out of reach of children

Please place it out of the reach of infants；If swallowed, get medical help or contact a Poison Control Center right away.

When using this product

FOR EXTERNAL USE ONIY

keep out of eyes. Rinse with water to remove.

INACTIVE INGREDIENT SECTON

water

uses and storage method

Apply one drop on clean skin before your moisturizer and smooth in gently all over face.

Caution: Keep out of reach of children and pets.

Avoidinginto eyes.

If you think you have sensitive skin,please test on a small area first.

Storage: Keep away from direct sun light or heat.